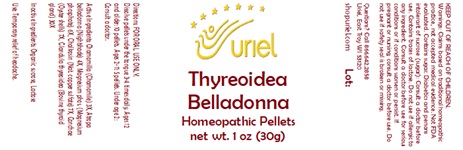 DRUG LABEL: Thyreoidea Belladonna
NDC: 48951-9356 | Form: PELLET
Manufacturer: Uriel Pharmacy, Inc.
Category: homeopathic | Type: HUMAN OTC DRUG LABEL
Date: 20231117

ACTIVE INGREDIENTS: OSTREA EDULIS SHELL 7 [hp_X]/1 1; MAGNESIUM PHOSPHATE, TRIBASIC, PENTAHYDRATE 6 [hp_X]/1 1; CHAMOMILE 3 [hp_X]/1 1; CUPRIC SULFATE 7 [hp_X]/1 1; THYROID, UNSPECIFIED 30 [hp_X]/1 1; ATROPA BELLADONNA 4 [hp_X]/1 1
INACTIVE INGREDIENTS: LACTOSE, UNSPECIFIED FORM; SUCROSE

Thyreoidea Belladonna

INDICATIONS AND USAGE

Directions: FOR ORAL USE ONLY.

DOSAGE AND ADMINISTRATION

Dissolve pellets under the tongue 3-4 times daily. Ages 12 and older: 10 pellets. Ages 2-11: 5 pellets. Under age 2: Consult a doctor.

ACTIVE INGREDIENT

Active Ingredients: Chamomilla (Chamomile) 3X, Atropa belladonna (Nightshade) 4X, Magnesium phos. (Magnesium phosphate) 6X, Chalkosin (Nat. copper sulfate) 7X, Conchae (Oyster shells) 7X, Glandula thyreoidea (Bovine thyroid gland) 30X

Inactive Ingredients: Organic sucrose, Lactose

PURPOSE

Use: Temporary relief of headache.

KEEP OUT OF REACH OF CHILDREN.

WARNINGS

Warnings: Claims based on traditional homeopathic practice, not accepted medical evidence. Not FDA evaluated. Contains sugar. Diabetics and persons intolerant of sucrose (sugar): Consult a doctor before use. Contains traces of lactose. Do not use if allergic to any ingredient. Consult a doctor before use for serious conditions or if conditions worsen or persist. If pregnant or nursing, consult a doctor before use. Do not use if safety seal is broken or missing.

Questions? Call 866.642.2858
Uriel, East Troy WI 53120
shopuriel.com Lot: